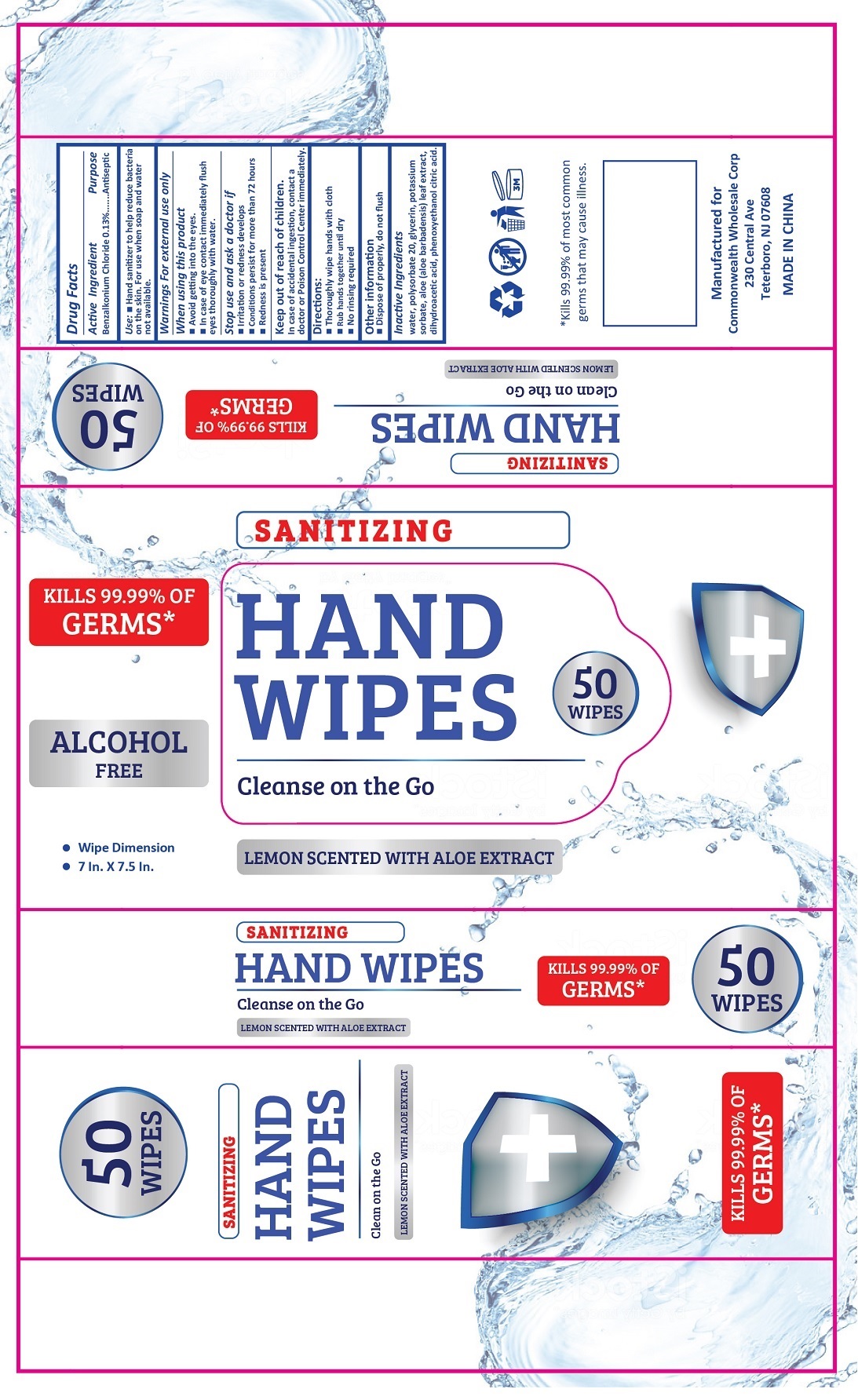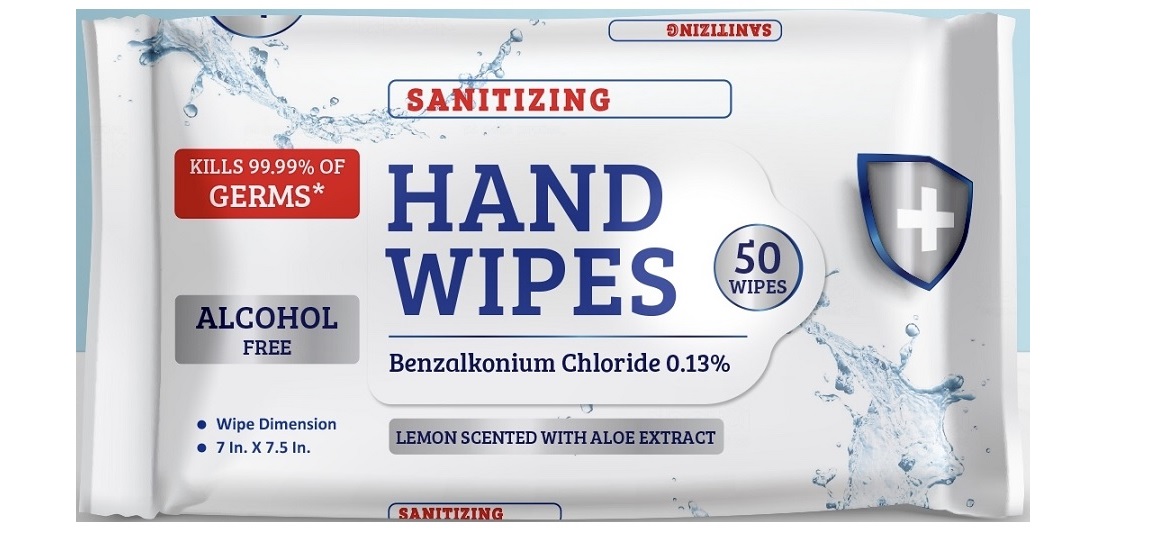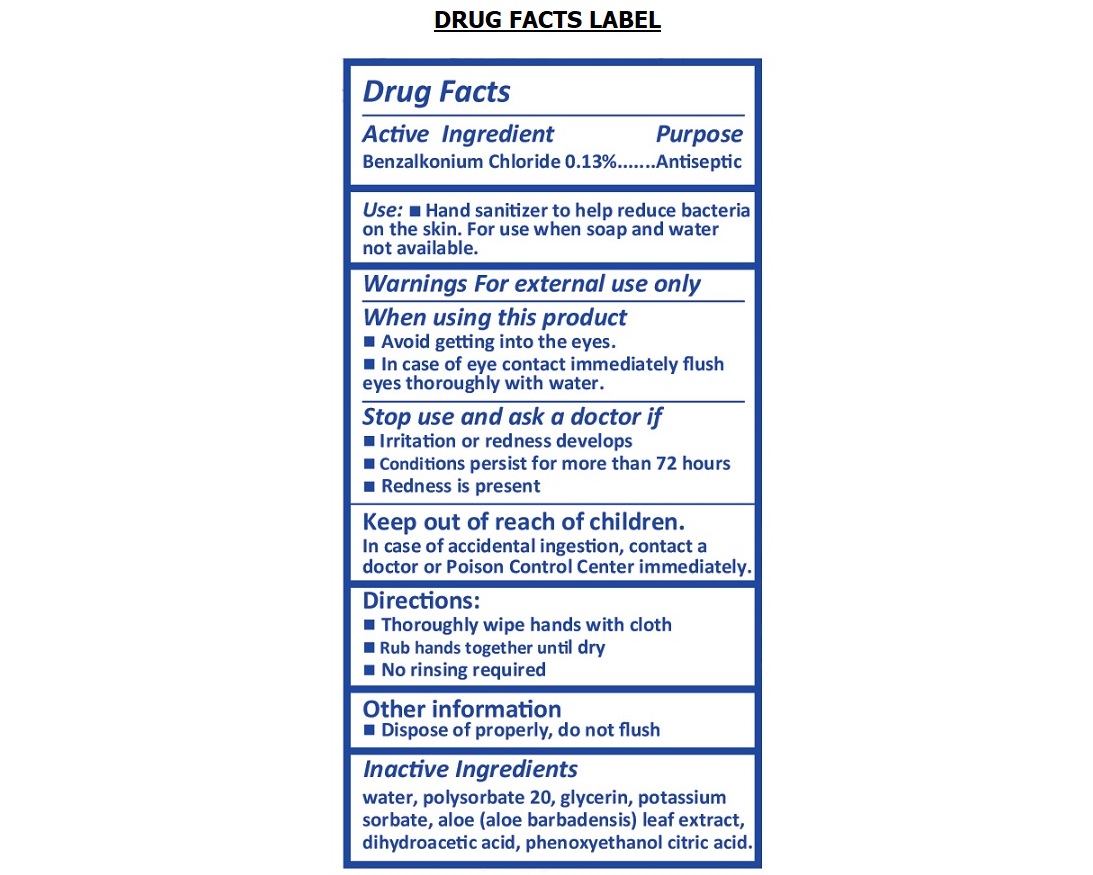 DRUG LABEL: Hand Wipes
NDC: 80408-619 | Form: CLOTH
Manufacturer: Ningbo Alabama Trading LLC
Category: otc | Type: HUMAN OTC DRUG LABEL
Date: 20200923

ACTIVE INGREDIENTS: BENZALKONIUM CHLORIDE 0.13 g/100 g
INACTIVE INGREDIENTS: WATER; POLYSORBATE 20; GLYCERIN; POTASSIUM SORBATE; ALOE VERA LEAF; DEHYDROACETIC ACID; PHENOXYETHANOL; CITRIC ACID MONOHYDRATE

HAND WIPES Cleanse on the Go

Active Ingredient

Benzalkonium Chloride 0.13%

Purpose

Antiseptic

INDICATIONS AND USAGE

Use: • Hand sanitizer to help reduce bacteria on the skin. For use when soap and water not available.

Warnings For external use only

When using this product

• Avoid getting into the eyes.

• In case of eye contact immediately flush eyes thoroughly with water.

Stop use and ask a doctor if

• Irritation or redness develops

• Condition persist for more than 72 hours

• Redness is present

Keep out of reach of children.

In case of accidental ingestion, contact a doctor or Poison Control Center immediately.

Directions:

• Thoroughly wipe hands with cloth

• Rub hands together until dry

• No rinsing required

Other information

• Dispose of properly, do not flush

Inactive Ingredients

water, polysorbate 20, glycerin, potassium sorbate, aloe (aloe barbadensis) leaf extract, dehydroacetic acid, phenoxyethanol citric acid.

SANITIZING

Cleanse on the Go

LEMON SCENTED WITH ALOE EXTRACT

KILLS 99.99% OF GERMS*

ALCOHOL FREE

*Kills 99.99% of most common germs that may cause illness.

Manufactured for

Commonwealth Wholesale Corp

230 Central Ave

Teterboro, NJ 07608

MADE IN CHINA